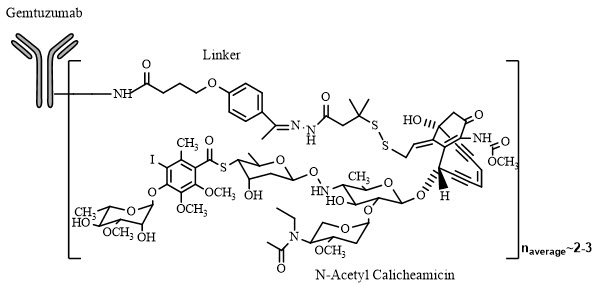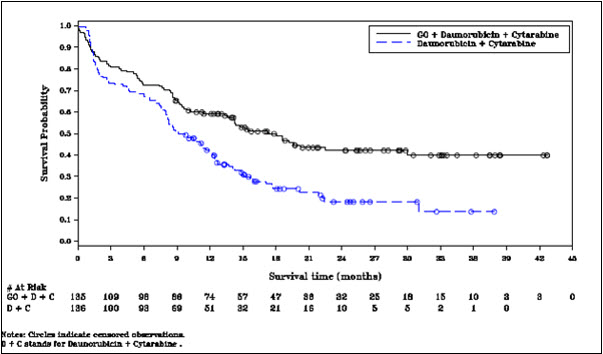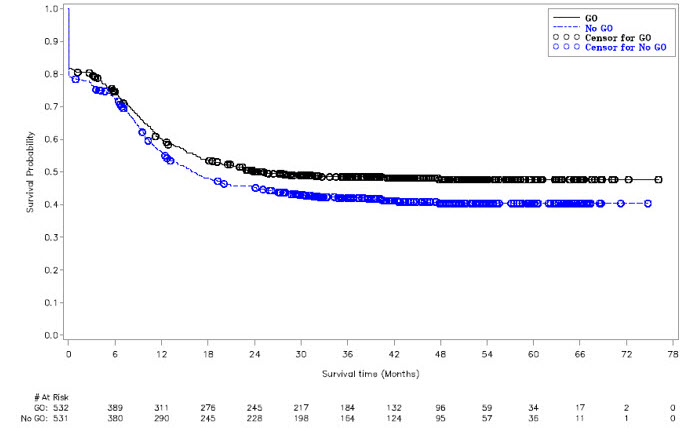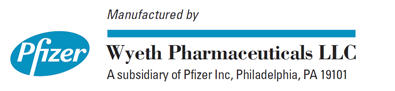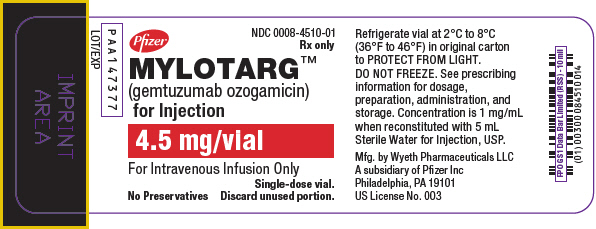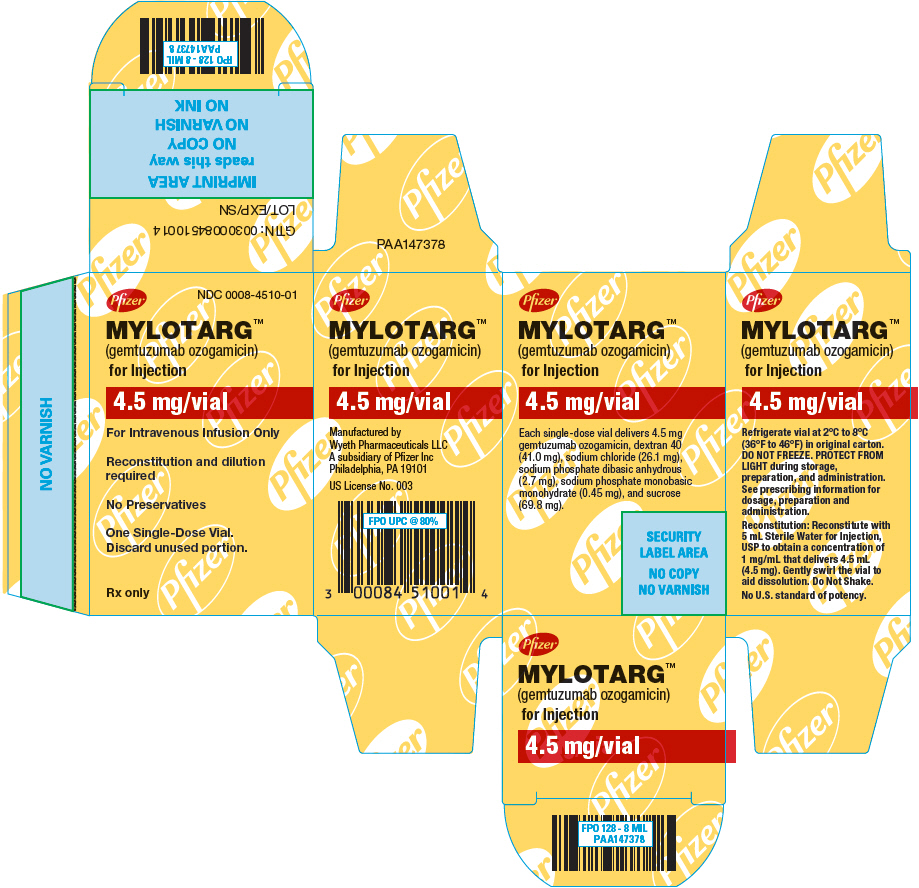 DRUG LABEL: Mylotarg
NDC: 0008-4510 | Form: INJECTION, POWDER, LYOPHILIZED, FOR SOLUTION
Manufacturer: Wyeth Pharmaceuticals LLC, a subsidiary of Pfizer Inc.
Category: prescription | Type: HUMAN PRESCRIPTION DRUG LABEL
Date: 20251219

ACTIVE INGREDIENTS: GEMTUZUMAB OZOGAMICIN 5 mg/5 mL
INACTIVE INGREDIENTS: DEXTRAN 40; SUCROSE; SODIUM CHLORIDE; SODIUM PHOSPHATE, MONOBASIC, UNSPECIFIED FORM; SODIUM PHOSPHATE, DIBASIC, UNSPECIFIED FORM

HIGHLIGHTS OF PRESCRIBING INFORMATION

These highlights do not include all the information needed to use MYLOTARG safely and effectively. See full prescribing information for MYLOTARG.
MYLOTARG™ (gemtuzumab ozogamicin) for injection, for intravenous use
Initial U.S. Approval: 2000

WARNING: HEPATOTOXICITY

See full prescribing information for complete boxed warning.

Hepatotoxicity, including severe or fatal hepatic veno-occlusive disease (VOD), also known as sinusoidal obstruction syndrome (SOS), has been reported in association with the use of MYLOTARG. (5.1, 6.1)

RECENT MAJOR CHANGES

Dosage and Administration, Instructions for Reconstitution, Dilution, and Administration (2.4) | 08/2021

1 INDICATIONS AND USAGE

MYLOTARG is a CD33-directed antibody and cytotoxic drug conjugate indicated for:

- treatment of newly-diagnosed CD33-positive acute myeloid leukemia (AML) in adults and pediatric patients 1 month and older (1.1).
- treatment of relapsed or refractory CD33-positive AML in adults and pediatric patients 2 years and older (1.2).

2 DOSAGE AND ADMINISTRATION

- Newly-diagnosed, de novo AML (combination regimen)
  Adults:
  - Induction: 3 mg/m^2 (up to one 4.5 mg vial) on Days 1, 4, and 7 in combination with daunorubicin and cytarabine (2.2).
  - Consolidation: 3 mg/m^2 on Day 1 (up to one 4.5 mg vial) in combination with daunorubicin and cytarabine (2.2).
Pediatric patients 1 month and older:
  1. 3 mg/m^2 for patients with body surface area (BSA) 0.6 m^2 or greater (2.2).
  2. 0.1 mg/kg for patients with BSA less than 0.6 m^2 (2.2).
  3. See Full Prescribing Information for complete dosing information (2.2).
- Newly-diagnosed AML (single-agent regimen):
  Adults:
  - Induction: 6 mg/m^2 (not limited to one 4.5 mg vial) on Day 1 and 3 mg/m^2 (not limited to one 4.5 mg vial) on Day 8 (2.2).
  - Continuation: For patients without evidence of disease progression following induction, up to 8 continuation courses of MYLOTARG 2 mg/m^2 (not limited to one 4.5 mg vial) on Day 1 every 4 weeks (2.2).
- Relapsed or refractory AML (single-agent regimen):
Adults and pediatric patients 2 years and older:
  1. 3 mg/m^2 (up to one 4.5 mg vial) on Days 1, 4, and 7 (2.2).
- Premedicate with a corticosteroid, antihistamine, and acetaminophen (2.1).

3 DOSAGE FORMS AND STRENGTHS

For Injection: 4.5 mg as a lyophilized cake or powder in a single-dose vial for reconstitution and dilution (3).

4 CONTRAINDICATIONS

Hypersensitivity to MYLOTARG or any of its components (4).

5 WARNINGS AND PRECAUTIONS

- Infusion-related reactions (including anaphylaxis): Premedicate with a corticosteroid, acetaminophen, and diphenhydramine. Monitor patients during and for at least 1 hour after the end of the infusion. Interrupt the infusion, administer steroids or antihistamines, or permanently discontinue treatment as necessary (2.1, 5.2, 6).
- Hemorrhage: Severe, including fatal, hemorrhage may occur when MYLOTARG is used at recommended doses. Monitor platelet counts frequently (5.3, 6.1).
- Embryo-fetal toxicity: Can cause fetal harm. Advise patients of reproductive potential of the potential risk to a fetus and to use effective contraception (5.6, 8.1, 8.3).

6 ADVERSE REACTIONS

The most common adverse reactions (greater than 15%) were hemorrhage, infection, fever, nausea, vomiting, constipation, headache, increased AST, increased ALT, rash, mucositis, febrile neutropenia, and decreased appetite (6).
To report SUSPECTED ADVERSE REACTIONS, contact Pfizer Inc. at 1-800-438-1985 or FDA at 1-800-FDA-1088 or www.fda.gov/medwatch.

8 USE IN SPECIFIC POPULATIONS

Lactation: Advise not to breastfeed (8.2).

FULL PRESCRIBING INFORMATION

WARNING: HEPATOTOXICITY

Hepatotoxicity, including severe or fatal hepatic veno-occlusive disease (VOD), also known as sinusoidal obstruction syndrome (SOS), has been reported in association with the use of MYLOTARG as a single agent, and as part of a combination chemotherapy regimen. Monitor frequently for signs and symptoms of VOD after treatment with MYLOTARG. (5.1 and 6.1)

1 INDICATIONS AND USAGE

1.1 Newly-Diagnosed CD33-positive Acute Myeloid Leukemia (AML)

MYLOTARG is indicated for the treatment of newly-diagnosed CD33-positive acute myeloid leukemia in adults and pediatric patients 1 month and older.

1.2 Relapsed or Refractory CD33-positive AML

MYLOTARG is indicated for the treatment of relapsed or refractory CD33-positive acute myeloid leukemia in adults and pediatric patients 2 years and older.

2 DOSAGE AND ADMINISTRATION

2.1 Premedication and Special Considerations

- Premedicate adults with acetaminophen 650 mg orally and diphenhydramine 50 mg orally or intravenously 1 hour prior to MYLOTARG dosing and 1 mg/kg methylprednisolone or an equivalent dose of an alternative corticosteroid within 30 minutes prior to infusion of MYLOTARG.
- Premedicate pediatric patients 1 month and older with acetaminophen 15 mg/kg (maximum of 650 mg) and diphenhydramine 1 mg/kg (maximum of 50 mg) 1 hour prior to MYLOTARG dosing, and 1 mg/kg methylprednisolone orally or intravenously within 30 minutes prior to infusion of MYLOTARG; additional doses of acetaminophen and diphenhydramine may be administered every 4 hours after the initial pretreatment dose. Repeat with the same dose of methylprednisolone or an equivalent corticosteroid for any sign of an infusion reaction, such as fever, chills, hypotension, or dyspnea during the infusion or within 4 hours afterwards [see Warnings and Precautions (5.2)].
- Use appropriate measures to prevent tumor lysis syndrome.
- For patients with hyperleukocytosis (leukocyte count greater than or equal to 30 Gi/L), cytoreduction is recommended prior to administration of MYLOTARG.

2.2 Recommended Dosage

Newly-Diagnosed De Novo CD33-positive AML (Combination Regimen)

Adults

The recommended dose of MYLOTARG in adults is 3 mg/m^2. A treatment course including MYLOTARG in combination therapy for adults with newly-diagnosed de novo CD33-positive AML consists of 1 induction cycle and 2 consolidation cycles [see Clinical Studies (14.1)].

For the induction cycle, the recommended dose of MYLOTARG is 3 mg/m^2 (up to one 4.5 mg vial) on Days 1, 4, and 7 in combination with daunorubicin and cytarabine. For patients requiring a second induction cycle, do NOT administer MYLOTARG during the second induction cycle.

For the consolidation cycles, the recommended dose of MYLOTARG is 3 mg/m^2 on Day 1 (up to one 4.5 mg vial) in combination with daunorubicin and cytarabine.

Pediatric Patients 1 Month and Older

The recommended dose of MYLOTARG in pediatric patients 1 month and older is:

- 3 mg/m^2 for patients with body surface area (BSA) greater than or equal to 0.6 m^2
- 0.1 mg/kg for patients with BSA less than 0.6 m^2

For Induction 1, MYLOTARG is given once in combination with standard chemotherapy. No MYLOTARG is given in the second induction cycle [see Clinical Studies (14.1)].

No MYLOTARG is given in the first or third intensification cycles. For Intensification 2, MYLOTARG is given once in combination with standard chemotherapy. Consider the risks and potential benefits before giving MYLOTARG during Intensification 2 [see Adverse Reactions (6.1)].

Newly-Diagnosed CD33-positive AML (Single-agent Regimen)

A treatment course of MYLOTARG as a single agent for adults with newly-diagnosed CD33-positive AML consists of 1 cycle of induction and up to 8 cycles of continuation therapy [see Clinical Studies (14.1)].

For the induction cycle, the recommended dose of MYLOTARG is 6 mg/m^2 (not limited to one 4.5 mg vial) as a single agent on Day 1, and 3 mg/m^2 (not limited to one 4.5 mg vial) on Day 8.

For continuation, the recommended dose of MYLOTARG is 2 mg/m^2 (not limited to one 4.5 mg vial) as a single agent on Day 1 every 4 weeks.

Relapsed or Refractory CD33-positive AML (Single-agent Regimen)

The recommended dose of MYLOTARG as a single agent for treatment for adults and pediatric patients 2 years and older with relapsed or refractory CD33-positive AML is 3 mg/m^2 (up to one 4.5 mg vial) on Days 1, 4, and 7. Treatment in the relapsed or refractory setting consists of a single course of MYLOTARG [see Clinical Studies (14.2)].

2.3 Dosage Modifications for Toxicities

Monitor blood counts frequently through resolution of cytopenias. Monitor blood counts and chemistries at least three times per week through recovery from treatment-related toxicities. Management of some adverse reactions [see Warnings and Precautions (5), Adverse Reactions (6)] may require dose interruptions or permanent discontinuation of MYLOTARG. Table 1 shows the dose modification guidelines for hematologic and nonhematologic toxicities.

Table 1. Dosage Modifications for Hematologic and Nonhematologic Toxicities
Hematologic and Nonhematologic Toxicities | Recommended Action
For patients receiving MYLOTARG in combination therapy
Persistent thrombocytopenia | - Adults: If platelet count does not recover to greater than or equal to 100 Gi/L within 14 days following the planned start date of the consolidation cycle (14 days after hematologic recovery following previous cycle), discontinue MYLOTARG (do not administer MYLOTARG in the consolidation cycles). - Pediatrics: Patients should have a platelet count of 75 Gi/L before the next cycle (induction or intensification).
Persistent neutropenia | - Adults: If neutrophil count does not recover to greater than 0.5 Gi/L within 14 days following the planned start date of the consolidation cycle (14 days after hematologic recovery following previous cycle), discontinue MYLOTARG (do not administer MYLOTARG in the consolidation cycles). - Pediatrics: Patients should have a neutrophil count of 1 Gi/L before the next cycle (induction or intensification).
For all patients receiving MYLOTARG (Monotherapy or in Combination)
VOD | - Discontinue MYLOTARG [see Warnings and Precautions (5.1)].
Total bilirubin greater than 2 × ULN, or AST and/or ALT greater than 2.5 × ULN | - Delay treatment with MYLOTARG until recovery of total bilirubin to less than or equal to 2 × ULN and AST and ALT to less than or equal to 2.5 × ULN prior to each dose. - Omit scheduled dose if delayed more than 2 days between sequential infusions.
Infusion-related reactions | - Interrupt the infusion and institute appropriate medical management. - Administer acetaminophen, diphenhydramine and/or methylprednisolone, if needed [see Dosage and Administration (2.1)] - Provide supportive care measures as needed. - For mild, moderate or severe infusion-related reactions, once symptoms resolve, consider resuming the infusion at no more than half the rate at which the reaction occurred. Repeat the procedure above in the event of recurrence of symptoms. - Permanently discontinue MYLOTARG upon occurrence of a severe infusion reaction or for any life-threatening infusion reaction [see Warnings and Precautions (5.2)].
Other severe or life-threatening non-hematologic toxicities | - Delay treatment with MYLOTARG until recovery to a severity of no more than mild. - Omit scheduled dose if delayed more than 2 days between sequential infusions.
Abbreviations: ALT=alanine aminotransferase; AST=aspartate aminotransferase; VOD=veno-occlusive disease; ULN=upper limit of normal.

2.4 Instructions for Reconstitution, Dilution, and Administration

Use appropriate aseptic technique for the reconstitution and dilution procedures. Protect the reconstituted and diluted MYLOTARG solution from light.

Reconstitution

- MYLOTARG is a cytotoxic drug. Follow applicable special handling and disposal procedures.^1
- Calculate the dose (mg) and number of vials of MYLOTARG required.
- Prior to reconstitution, allow drug product vials to reach room temperature (up to 30°C) for approximately 5 minutes.
- Reconstitute each vial with 5 mL of Sterile Water for Injection, USP to obtain a concentration of 1 mg/mL of MYLOTARG that delivers 4.5 mL (4.5 mg).
- Gently swirl the vial to aid dissolution. DO NOT SHAKE.
- Inspect the reconstituted solution for particulates and discoloration. The reconstituted solution may contain small white to off-white, opaque to translucent, and amorphous to fiber-like particles.
- MYLOTARG contains no bacteriostatic preservatives.
- If the reconstituted solution cannot be used immediately, it may be stored in the original vial for up to 16 hours in a refrigerator (2°C to 8°C; 36°F to 46°F) or up to 3 hours at room temperature (up to 30°C).
  PROTECT FROM LIGHT. DO NOT FREEZE.

Dilution

- Calculate the required volume of the reconstituted solution needed to obtain the appropriate dose according to patient body surface area. Withdraw this amount from the vial(s) using a syringe. PROTECT FROM LIGHT. Discard any unused reconstituted solution left in the vial.

Doses must be mixed to a concentration between 0.075 mg/mL to 0.234 mg/mL according to the following instructions:

- Doses less than 3.9 mg must be prepared for administration by syringe. Add the reconstituted MYLOTARG solution to a syringe with 0.9% Sodium Chloride Injection to a final concentration between 0.075 mg/mL to 0.234 mg/mL. PROTECT FROM LIGHT.
- Doses greater than or equal to 3.9 mg are to be diluted in a syringe or a polyvinyl chloride (PVC) with di(2-ethylhexyl)phthalate (DEHP), non-PVC polyolefin, or ethylene vinyl acetate intravenous infusion bag in an appropriate volume of 0.9% Sodium Chloride Injection to ensure a final concentration between 0.075 mg/mL to 0.234 mg/mL. PROTECT FROM LIGHT.
- Gently invert the infusion container to mix the diluted solution. DO NOT SHAKE.
- Following dilution with 0.9% Sodium Chloride Injection, MYLOTARG solution should be infused immediately. If not used immediately, the diluted solution may be stored up to 18 hours in a refrigerator (2°C to 8°C; 36°F to 46°F) and for up to 6 hours at room temperature (up to 30°C). The allowed time at room temperature (up to 30°C) includes the time required for preparation of the diluted solution, equilibration, if needed, and the 2 hours needed to administer to the patient. PROTECT FROM LIGHT and DO NOT FREEZE.

Administration

- Use an in-line 0.2 micron polyethersulfone (PES) filter for infusion of MYLOTARG.
- Protect the intravenous bag from light using a light-blocking cover during infusion. The infusion line does not need to be protected from light.
- Infuse the diluted solution over 2 hours using an infusion set made of polyvinyl chloride (PVC) with DEHP, PVC non-DEHP, polyethylene, or polyurethane. The infusion must be completed prior to the end of the allowed 6-hour storage of the diluted solution at room temperature (up to 30°C).
- Do not mix MYLOTARG with, or administer as an infusion with, other medicinal products.

3 DOSAGE FORMS AND STRENGTHS

For injection: 4.5 mg as a white to off-white lyophilized cake or powder in a single-dose vial for reconstitution and further dilution.

4 CONTRAINDICATIONS

MYLOTARG is contraindicated in patients with a history of hypersensitivity to the active substance in MYLOTARG or any of its components or to any of the excipients. Reactions have included anaphylaxis [see Warnings and Precautions (5.2), Adverse Reactions (6)].

5 WARNINGS AND PRECAUTIONS

5.1 Hepatotoxicity, Including Veno-occlusive Liver Disease (VOD)

Hepatotoxicity, including life-threatening and sometimes fatal hepatic VOD events, have been reported in patients receiving MYLOTARG as a single agent or as part of a combination chemotherapy regimen [see Adverse Reactions (6)].

In ALFA-0701, VOD events were reported in 6/131 (5%) adult patients during or following treatment with MYLOTARG, or following later hematopoietic stem cell transplantation (HSCT). The median time from the MYLOTARG dose to onset of VOD was 9 days (range: 2–298 days), with 5 events occurring within 28 days of any dose of MYLOTARG and 1 event occurring greater than 28 days after the last dose of MYLOTARG. Three of the 6 VOD events were fatal. VOD was also reported in 2 patients in the control arm of ALFA-0701 after receiving MYLOTARG as a therapy for relapsed AML.

In MyloFrance-1 (MYLOTARG 3 mg/m^2 on Days 1, 4 and 7), VOD events were reported in none of the 57 patients during or following treatment, or following HSCT after completion of MYLOTARG treatment.

In AAML0531, VOD events were reported in 25/520 (5%) pediatric patients in the MYLOTARG arm. VOD was fatal in 2 patients. Among 187 pediatric patients who underwent HSCT in the MYLOTARG arm, VOD occurred within 30 days post-HSCT in 20 (11%) patients.

Based on an analysis across trials, the risk of VOD was higher in adult patients who received higher doses of MYLOTARG as monotherapy, in patients with moderate or severe hepatic impairment prior to receiving MYLOTARG, in patients treated with MYLOTARG after HSCT, and in patients who underwent HSCT after treatment with MYLOTARG. Patients who had moderate/severe hepatic impairment prior to treatment with MYLOTARG were 8.7 times more likely to develop VOD compared to patients without moderate/severe hepatic impairment at baseline. Patients treated with MYLOTARG for relapse after HSCT were 2.6 times more likely to develop VOD compared to patients without prior HSCT. Patients who underwent HSCT following MYLOTARG treatment were 2.9 times more likely to develop VOD after HSCT compared to patients without HSCT following MYLOTARG treatment. Although no relationship was found between VOD and time of HSCT relative to higher MYLOTARG monotherapy doses, the ALFA-0701 study recommended an interval of 2 months between the last dose of MYLOTARG and HSCT. In MyloFrance-1, no patients underwent HSCT within 3.5 months of MYLOTARG therapy.

Assess ALT, AST, total bilirubin, and alkaline phosphatase prior to each dose of MYLOTARG. After treatment with MYLOTARG, monitor frequently for signs and symptoms of VOD; these may include elevations in ALT, AST, total bilirubin, hepatomegaly (which may be painful), rapid weight gain, and ascites. Monitoring only total bilirubin may not identify all patients at risk of VOD. For patients who develop abnormal liver tests, more frequent monitoring of liver tests and clinical signs and symptoms of hepatotoxicity is recommended. For patients who proceed to HSCT, monitor liver tests frequently during the post-HSCT period, as appropriate.

Manage signs or symptoms of hepatic toxicity by dose interruption or discontinuation of MYLOTARG [see Dosage and Administration (2.3)]. In patients who experience VOD, discontinue MYLOTARG and treat according to standard medical practice.

5.2 Infusion-Related Reactions (Including Anaphylaxis)

Life-threatening or fatal infusion-related-reactions can occur during or within 24 hours following infusion of MYLOTARG [see Adverse Reactions (6)]. Signs and symptoms of infusion-related reactions may include fever, chills, hypotension, tachycardia, hypoxia and respiratory failure.

Premedicate prior to MYLOTARG infusion [see Dosage and Administration (2.1)]. Monitor vital signs frequently during infusion. Interrupt infusion immediately for patients who develop evidence of infusion reaction, especially dyspnea, bronchospasm, or hypotension. Monitor patients during and for at least 1 hour after the end of the infusion or until signs and symptoms completely resolve. Discontinue use of MYLOTARG in patients who develop signs or symptoms of anaphylaxis, including severe respiratory symptoms or clinically significant hypotension [see Dosage and Administration (2.2)].

5.3 Hemorrhage

MYLOTARG is myelosuppressive and can cause fatal or life-threatening hemorrhage due to prolonged thrombocytopenia. In ALFA-0701, (MYLOTARG in combination with chemotherapy), all grades and Grade 3–4 bleeding events were reported in 118/131 (90%) and 27/131 (21%) patients, respectively. Fatal bleeding events (including cerebral hematoma, intracranial hematoma, and subdural hematoma) occurred in 4/131 (3%) patients. Thrombocytopenia with platelet counts less than 50 Gi/L persisting more than 42 days occurred in 19 (19%) patients in the induction phase [see Adverse Reactions (6)]. The proportion of patients with persistent thrombocytopenia increased with progressive treatment phases and was higher in patients treated with MYLOTARG plus chemotherapy than with chemotherapy alone [see Adverse Reactions (6)].

In AAML0531, fatal bleeding occurred in 3/520 (<1%) of the pediatric patients. Grade 3 or 4 bleeding was reported in 66/520 (13%) of the pediatric patients in the MYLOTARG arm.

In AML-19 (MYLOTARG monotherapy at 6 mg/m^2 Day 1 and 3 mg/m^2 Day 8), all grades and Grade 3 or higher bleeding were reported in 28/111 (25%) and 14/111 (13%) patients, respectively. Fatal bleeding occurred in 1/111 (1%). In MyloFrance-1 (MYLOTARG 3 mg/m^2 as monotherapy), Grade 3 bleeding was reported in 4/57 (7%) patients, but no patient experienced Grade 4 hemorrhage.

Assess blood counts prior to each dose of MYLOTARG and monitor blood counts frequently after treatment with MYLOTARG until resolution of cytopenias. Monitor patients for signs and symptoms of bleeding during treatment with MYLOTARG. Manage severe bleeding, hemorrhage or persistent thrombocytopenia using dose delay or permanent discontinuation of MYLOTARG [see Dosage and Administration (2.2)], and provide supportive care per standard practice.

5.4 QT Interval Prolongation

QT interval prolongation has been observed in patients treated with other drugs containing calicheamicin. When administering MYLOTARG to patients who have a history of or predisposition for QTc prolongation, who are taking medicinal products that are known to prolong QT interval, and in patients with electrolyte disturbances, obtain electrocardiograms (ECGs) and electrolytes prior to the start of treatment and as needed during administration.

5.5 Use in AML with Adverse-Risk Cytogenetics

In subgroup analyses in ALFA-0701, the addition of MYLOTARG to standard combination chemotherapy did not improve event-free survival in the subgroup of patients having adverse-risk cytogenetics (HR 1.11; 95% CI: 0.63, 1.95). For patients being treated with MYLOTARG in combination with daunorubicin and cytarabine for newly-diagnosed de novo AML, when cytogenetics testing results become available consider whether the potential benefit of continuing treatment with MYLOTARG outweighs the risks for the individual patient.

5.6 Embryo-Fetal Toxicity

Based on its mechanism of action and findings from animal studies, MYLOTARG can cause embryo-fetal harm when administered to a pregnant woman. In animal studies, gemtuzumab ozogamicin caused embryo-fetal toxicity, starting at a dose that was approximately 0.4 times the exposure in patients at the maximum recommended dose, based on the area under the concentration-time curve (AUC).

Advise pregnant women of the potential risk to a fetus. Advise females of reproductive potential to use effective contraception during treatment with MYLOTARG and for at least 6 months after the final dose. Advise males with female partners of reproductive potential to use effective contraception during treatment with MYLOTARG and for at least 3 months after the last dose [see Use in Specific Populations (8.1, 8.3)].

6 ADVERSE REACTIONS

The following clinically significant adverse reactions are described elsewhere in the labeling:

- Hepatotoxicity, including VOD [see Warnings and Precautions (5.1)]
- Infusion-related reactions [see Warnings and Precautions (5.2)]
- Hemorrhage [see Warnings and Precautions (5.3)]

6.1 Clinical Trials Experience

Because clinical trials are conducted under widely varying conditions, adverse reaction rates observed in the clinical trials of a drug cannot be directly compared to rates in the clinical trials of another drug and may not reflect the rates observed in practice.

Combination Therapy in Newly-Diagnosed De Novo CD33-positive AML

The safety of MYLOTARG in first-line combination therapy was evaluated in two prospective clinical trials, Study ALFA-0701 in adults and Study AAML0531 in pediatric patients.

Study ALFA-0701

The safety evaluation of MYLOTARG (3 mg/m^2 Day 1, 4 and 7 in combination with daunorubicin and cytarabine [DA]) in adults is based on data from ALFA-0701 for 131 patients treated with MYLOTARG plus DA and in 137 patients treated with DA alone [see Clinical Studies (14.1)]. In this study, 123 patients received all 3 fractionated doses of MYLOTARG and 7 patients missed at least 1 dose, with a mean total dose administered during induction of 14.51 mg (range: 4.6–18.0). MYLOTARG was received by 91 (70%) patients in the MYLOTARG arm during Consolidation 1 and 64 (49%) patients in the MYLOTARG arm during Consolidation 2.

Safety data consisting of selected TEAEs considered most important for understanding the safety profile of MYLOTARG as well as all adverse events (AEs) that led to the permanent discontinuation of treatment were retrospectively collected. The selected TEAEs consisted of all grades hemorrhages, all grades VOD, and severe infections.

Discontinuation due to any adverse reaction occurred in 31% of patients in the MYLOTARG arm versus 7% in the DA arm. The most frequent (greater than or equal to 1%) adverse reactions for patients treated with MYLOTARG that led to permanent discontinuation were thrombocytopenia (15%), VOD (3%), and septic shock (2%).

Fatal adverse reactions occurred in 8 patients (6%) in the MYLOTARG arm versus 3 patients (2%) in the DA arm. In the MYLOTARG arm, 3 patients died of VOD, 4 patients died of hemorrhage-related events (CNS hemorrhage, hemorrhagic shock), and 1 patient died of suspected cardiac cause. In the DA arm, 3 patients died of sepsis.

Table 2. Selected Grade 3 and Higher Adverse Reactions in Patients with Newly-Diagnosed De Novo AML in ALFA-0701
 | MYLOTARG + Daunorubicin + Cytarabine (n, %) | Daunorubicin + Cytarabine (n, %)
Induction | N = 131 | N = 137
Infection [Infection is a grouped term consisting of multiple preferred terms.] | 61 (47%) | 53 (39%)
Hemorrhage [Hemorrhage is a grouped term consisting of multiple preferred terms.] | 24 (18%) | 12 (9%)
Veno-occlusive liver disease [Veno-occlusive liver disease includes the following reported PTs: Veno-occlusive liver disease, veno-occlusive disease.] | 3 (2%) | 0
Consolidation 1 | N = 91 | N = 103
Infection | 50 (55%) | 43 (42%)
Hemorrhage | 5 (5%) | 0
Veno-occlusive liver disease | 0 | 0
Consolidation 2 | N = 64 | N = 107
Infection | 32 (50%) | 54 (50%)
Hemorrhage | 4 (6%) | 0
Veno-occlusive liver disease | 0 | 0
Abbreviations: AML=acute myeloid leukemia; N=number of patients; PT=preferred term.

All patients in ALFA-0701 developed severe neutropenia, thrombocytopenia and anemia. The incidence of Grade 3–4 thrombocytopenia that was prolonged in the absence of active leukemia was higher in patients treated with MYLOTARG (Table 3).

Table 3. Prolonged Cytopenias [Platelets less than 50 Gi/L or neutrophils less than 0.5 Gi/L lasting past cycle Day 42 in the absence of active leukemia.] in ALFA-0701
 | MYLOTARG + Daunorubicin + Cytarabine (n/N, %) | Daunorubicin + Cytarabine (n/N, %)
Induction
Prolonged thrombocytopenia | 19/101 (19%) | 7/97 (7%)
Prolonged neutropenia | 3/106 (3%) | 0/101 (0%)
Consolidation 1
Prolonged thrombocytopenia | 21/87 (24%) | 6/91 (7%)
Prolonged neutropenia | 3/88 (3%) | 1/97 (1%)
Consolidation 2
Prolonged thrombocytopenia | 22/62 (35%) | 25/103 (24%)
Prolonged neutropenia | 1/62 (2%) | 2/105 (2%)

Table 4 summarizes shifts in selected chemistry abnormalities by treatment arm for patients treated in ALFA-0701.

Table 4. Chemistry Laboratory Values: Shifts in Subjects with Baseline Grade 2 or Lower Values in ALFA-0701
 | MYLOTARG + Daunorubicin + Cytarabine |  | Daunorubicin + Cytarabine
Laboratory Abnormality | Subjects (n) with baseline Grade less than or equal to 2 | Progressed to Grade greater than or equal to 3 (n, %) | Subjects (n) with baseline Grade less than or equal to 2 | Progressed to Grade greater than or equal to 3 (n, %)
Hypophosphatemia | 117 | 75 (64%) | 127 | 52 (41%)
Hypokalemia | 127 | 73 (57%) | 133 | 41 (31%)
Hyponatremia | 129 | 57 (44%) | 134 | 36 (27%)
Alkaline phosphatase increased | 120 | 16 (13%) | 128 | 7 (5%)
Aspartate aminotransferase increased | 126 | 18 (14%) | 132 | 11 (8%)
Alanine aminotransferase increased | 124 | 13 (10%) | 132 | 20 (15%)
Blood bilirubin increased | 119 | 9 (8%) | 126 | 5 (4%)

Study AAML0531

The safety evaluation of MYLOTARG in combination with chemotherapy in pediatric patients is based on data from AAML0531 [see Clinical Studies (14.1)] in randomized and treated patients (N = 520 MYLOTARG and chemotherapy and N = 517 chemotherapy alone). In the MYLOTARG arm of this study, 520 patients received Induction 1 and 326 patients received Intensification 2.

Safety data collected included only Grade 3 and 4 nonhematologic adverse events, deaths, VOD/SOS, and prolongation of neutropenia and thrombocytopenia.

Table 5 shows the Grade 3 or 4 adverse reactions (≥5%) in the MYLOTARG + chemotherapy or chemotherapy alone arms in patients with newly-diagnosed de novo AML in AAML0531.

In the MYLOTARG + chemotherapy arm, fatal adverse reactions (by grouped terms) were infection (14 [3%]), multi-organ failure (5 [1%]), anemia (1 [<1%]), and hemorrhage (3 [<1%]). In the chemotherapy arm, fatal adverse reactions included infection (7 [1%]), multi-organ failure (6 [1%]), hepatic failure (1 [<1%]), hypotension (3 [<1%]), and hemorrhage (3 [<1%]).

Table 5. Grade 3 and Higher Adverse Reactions (≥5%) in Patients with Newly-Diagnosed De Novo AML in AAML0531 During Treatment Cycles with MYLOTARG
 | Induction 1 |  | Intensification 2
 | MYLOTARG + Chemotherapy N = 520 n (%) | Chemotherapy alone N = 517 n (%) | MYLOTARG + Chemotherapy N = 326 n (%) | Chemotherapy alone N = 304 n (%)
Infection [Grouped term consisting of multiple preferred terms] | 186 (36%) | 181 (35%) | 220 (67%) | 211 (69%)
Febrile neutropenia | 167 (32%) | 157 (30%) | 79 (24%) | 68 (22%)
Decreased appetite | 78 (15%) | 79 (15%) | 61 (19%) | 36 (12%)
Hyperglycemia | 59 (11%) | 55 (11%) | 36 (11%) | 28 (9%)
Mucositis | 55 (11%) | 64 (12%) | 25 (8%) | 15 (5%)
Hypoxia | 35 (7%) | 26 (5%) | 19 (6%) | 22 (7%)
Hemorrhage | 36 (7%) | 19 (4%) | 19 (6%) | 9 (3%)
Transaminase Increased | 33 (6%) | 24 (5%) | 23 (7%) | 13 (4%)
Diarrhea | 21 (4%) | 36 (7%) | 15 (5%) | 10 (3%)
Nausea | 21 (4%) | 18 (4%) | 23 (7%) | 10 (3%)
Hypotension | 16 (3%) | 26 (5%) | 28 (9%) | 23 (8%)

The addition of MYLOTARG to chemotherapy was associated with a higher incidence of prolonged thrombocytopenia and neutropenia particularly when used in Intensification 2. During Intensification 2, prolonged thrombocytopenia (platelets <50 Gi/L lasting past cycle Day 42 in the absence of active leukemia) was reported in 64% (190/297) of patients in the MYLOTARG + chemotherapy arm compared with 55% (146/264) in the chemotherapy alone arm. Prolonged neutropenia (neutrophils <0.5 Gi/L lasting past cycle Day 42 in the absence of active leukemia) occurred in 47% (142/300) versus 43% (118/275) of patients, respectively. The prolonged cytopenias were associated with more deaths in remission in the MYLOTARG + chemotherapy arm (29 [5%]) compared to the chemotherapy alone arm (15 [3%]).

VOD events were reported in 25 (5%) patients in the MYLOTARG + chemotherapy arm as well as 25 (5%) of the chemotherapy alone arm. VOD was fatal in 2 (<1%) and 7 (1%) patients in the MYLOTARG + chemotherapy arm and chemotherapy alone arm, respectively.

Monotherapy for Newly-Diagnosed CD33-positive AML

The safety evaluation of MYLOTARG (6 mg/m^2 then 3 mg/m^2, with 7 days between the doses) as monotherapy is based on a randomized, open-label, Phase 3 trial of MYLOTARG (N=118) versus best supportive care (BSC) (N=119) in patients with previously untreated AML who were considered ineligible for intensive chemotherapy in Study AML-19 [see Clinical Studies (14.1)].

The overall incidence of any Grade adverse reactions reported in AML-19 was 87% in the MYLOTARG arm and 90% in the BSC arm. The incidence of Grade greater than or equal to 3 adverse reactions was 61% in the MYLOTARG arm and 68% in the BSC arm. Death due to any Adverse Event was reported in the MYLOTARG arm of 19 (17%) compared to the BSC arm of 23 (20%).

Table 6. Selected Adverse Reactions in AML-19
 | MYLOTARG n=111 |  | Best Supportive Care n=114
 | Any Grade | Grade ≥3 | Any Grade | Grade ≥3
Liver | 57 (51%) | 8 (7%) | 52 (46%) | 7 (6%)
Fatigue | 51 (46%) | 13 (12%) | 69 (61%) | 24 (21%)
Infection | 49 (44%) | 39 (35%) | 48 (42%) | 39 (34%)
Cardiac | 31 (28%) | 7 (6%) | 37 (33%) | 16 (14%)
Bleeding | 28 (25%) | 14 (13%) | 34 (30%) | 14 (12%)
Febrile neutropenia | 20 (18%) | 20 (18%) | 27 (24%) | 27 (24%)
Metabolic | 18 (16%) | 4 (4%) | 17 (15%) | 7 (6%)
Renal | 7 (6%) | 4 (4%) | 9 (8%) | 5 (4%)

Monotherapy for Relapsed or Refractory CD33-positive AML

The adverse reactions described in this section reflect exposure to MYLOTARG 3 mg/m^2 on Days 1, 4 and 7 as monotherapy in 57 patients with relapsed AML treated on MyloFrance-1 [see Clinical Studies (14.1)]. All 57 (100%) patients received the 3 planned doses of MYLOTARG.

During the treatment period, Grade 3 treatment-emergent adverse events (TEAEs) that occurred in greater than 1% patients included sepsis (32%), fever (16%), rash (11%), pneumonia (7%), bleeding (7%), mucositis (4%), pain (4%), diarrhea (2%), headaches (2%), tachycardia (2%), and lung edema (2%). No Grade 4 toxicity was observed. All grade TEAEs that occurred in greater than 15% of patients included fever (79%), infection (42%), increased AST (40%), bleeding (23%), nausea and vomiting (21%), constipation (21%), mucositis (21%), headache (19%), increased ALT (16%), and rash (16%). No infectious deaths occurred. Grade 1 or 2 hyperbilirubinemia developed in 4 (7%) patients. No episodes of VOD occurred. Seven patients received HSCT after MYLOTARG treatment. Three patients received an allogeneic BMT and 4 patients were treated with autologous BMT. No patients developed VOD following HSCT.

6.2 Postmarketing Experience

The following adverse drug reactions have been identified during post-approval use of MYLOTARG. Because these reactions are reported voluntarily from a population of uncertain size, it is not always possible to reliably estimate their frequency or establish a causal relationship to drug exposure.

Gastrointestinal Disorders: Neutropenic colitis [including fatal events]

Infections and Infestations: fungal lung infections including Pulmonary mycosis and Pneumocystis jirovecii pneumonia; and bacterial infections including Stenotrophomonas infection

Renal and Urinary Disorders: Hemorrhagic cystitis

Respiratory, Thoracic and Mediastinal Disorders: Interstitial pneumonia

6.3 Immunogenicity

As with all therapeutic proteins, there is potential for immunogenicity. Immunogenicity of MYLOTARG was not studied in clinical trials using the recommended dose regimens.

8 USE IN SPECIFIC POPULATIONS

8.1 Pregnancy

Risk Summary

Based on its mechanism of action and findings from animal studies [see Clinical Pharmacology (12.1), Nonclinical Toxicology (13.1)], MYLOTARG can cause embryo-fetal harm when administered to a pregnant woman. There are no available data on MYLOTARG use in pregnant women to evaluate for a drug-associated risk. In animal reproduction studies, gemtuzumab ozogamicin caused embryo-fetal toxicity, including structural abnormalities and alterations to growth, at maternal systemic exposures that were greater than or equal to 0.4 times the exposure in patients at the maximum recommended dose based on AUC (see Data). Advise pregnant women of the potential risk to a fetus.

The estimated background risk of major birth defects and miscarriage for the indicated population is unknown. All pregnancies have a background risk of birth defect, loss, or other adverse outcomes. In the U.S. general population, the estimated background risk of major birth defects and miscarriage in clinically recognized pregnancies is 2–4% and 15–20%, respectively.

Data

Animal Data

In an embryo-fetal development study in rats, pregnant animals received daily intravenous doses up to 1.2 mg/m^2/day gemtuzumab ozogamicin during the period of organogenesis. Embryo-fetal toxicities including fetal growth retardation as evidenced by decreased live fetal weights, incidence of fetal wavy ribs and delayed skeletal ossification were observed at greater than or equal to 0.15 mg/m^2/day. Increased embryo-fetal lethality and fetal morphological anomalies (digital malformations, absence of the aortic arch, anomalies in the long bones in the forelimbs, misshapen scapula, absence of a vertebral centrum, and fused sternebrae) were observed at greater than or equal to 0.36 mg/m^2/day. All doses with embryo-fetal effects were observed in the presence of maternal toxicity that included decreases in gestational body weight gain, food consumption, and gravid uterine weight. The lowest dose at which embryo-fetal effects were observed in rats (0.15 mg/m^2/day) was 0.4 times the exposure in patients at the maximum recommended human dose, based on AUC.

8.2 Lactation

Risk Summary

There are no data on the presence of gemtuzumab ozogamicin or its metabolites in human milk, the effects on the breastfed infant, or the effects on milk production. Because of the potential for serious adverse reactions in the breastfed infant, advise women not to breastfeed during treatment with MYLOTARG and for at least 1 month after the final dose.

8.3 Females and Males of Reproductive Potential

MYLOTARG can cause embryo-fetal harm when administered to a pregnant woman [see Use in Specific Populations (8.1)].

Pregnancy Testing

Verify the pregnancy status in females of reproductive potential prior to initiating MYLOTARG.

Contraception

Females

Advise females of reproductive potential to use effective contraception during treatment with MYLOTARG and for at least 6 months after the last dose [see Nonclinical Toxicology (13.1)].

Males

Advise males with female partners of reproductive potential to use effective contraception during treatment with MYLOTARG and for at least 3 months after the last dose [see Nonclinical Toxicology (13.1)].

Infertility

Females

Based on findings in animals, MYLOTARG may impair female fertility [see Nonclinical Toxicology (13.1)].

Males

Based on findings in animals, MYLOTARG may impair male fertility [see Nonclinical Toxicology (13.1)].

8.4 Pediatric Use

The safety and effectiveness of MYLOTARG in combination with standard chemotherapy have been established in pediatric patients 1 month and older with newly-diagnosed de novo AML. The use of MYLOTARG for this indication is supported by evidence of effectiveness from adequate and well-controlled studies in adults with supportive data on safety and effectiveness in Study AAML0531 (NCT00372593) [see Adverse Reactions (6.1), Clinical Studies (14.1)]. AAML0531 included patients in the following age groups: 2 patients less than 27 days old, 94 patients 28 days to less than 2 years old, 225 patients 2 years to less than 12 years old, 175 patients 12 years old to less than 18 years old, and 36 patients 18 years or older in the MYLOTARG plus chemotherapy arm. The safety and effectiveness of MYLOTARG with standard chemotherapy in pediatric patients less than 1 month of age with newly-diagnosed de novo AML have not been established.

The safety and effectiveness of MYLOTARG as a single agent in pediatric patients with newly-diagnosed AML have not been established.

The safety and effectiveness of MYLOTARG as a single agent in the pediatric patients with relapsed or refractory AML is supported by a single-arm trial in 29 patients in the following age groups: 1 patient 1 month to less than 2 years old, 13 patients 2 years to less than 12 years old, and 15 patients 12 years to 18 years old. A literature review included an additional 96 patients with ages ranging from 0.2 to 21 years. No differences in efficacy and safety were observed by age. The information on this use is discussed throughout the labeling. The safety and effectiveness of MYLOTARG as a single agent in pediatric patients less than 2 years of age with relapsed or refractory AML have not been established.

8.5 Geriatric Use

Use of MYLOTARG in combination with daunorubicin and cytarabine in newly-diagnosed adult patients with de novo AML is supported by a randomized, controlled trial that included 50 patients greater than or equal to 65 years old. No overall differences in safety or effectiveness were observed between these subjects and younger subjects. Use of MYLOTARG monotherapy in newly-diagnosed adult patients with AML is supported by a randomized controlled trial with 118 patients treated with MYLOTARG. All patients were over the age of 60 years and 65% of patients were above 75 years. No overall differences in effectiveness were observed by age.

Use of MYLOTARG as single-agent treatment of relapsed or refractory AML is supported by a single-arm trial that included 27 patients 65 years or older. No overall differences in effectiveness were observed between these patients and younger patients. Elderly patients experienced a higher rate of fever and severe or greater infections.

11 DESCRIPTION

Gemtuzumab ozogamicin is an antibody-drug conjugate (ADC) composed of the CD33-directed monoclonal antibody (hP67.6; recombinant humanized immunoglobulin [Ig] G4, kappa antibody produced by mammalian cell culture in NS0 cells) that is covalently linked to the cytotoxic agent N-acetyl gamma calicheamicin. Gemtuzumab ozogamicin consists of conjugated and unconjugated gemtuzumab. The conjugated molecules differ in the number of activated calicheamicin derivative moieties attached to gemtuzumab. The number of conjugated calicheamicin derivatives per gemtuzumab molecule ranges from predominantly zero to 6, with an average of 2 to 3 moles of calicheamicin derivative per mole of gemtuzumab.

MYLOTARG (gemtuzumab ozogamicin) for injection is supplied as a sterile, white to off-white, preservative-free lyophilized cake or powder for intravenous administration. Each single-dose vial delivers 4.5 mg gemtuzumab ozogamicin. Inactive ingredients are dextran 40 (41.0 mg), sodium chloride (26.1 mg), sodium phosphate dibasic anhydrous (2.7 mg), sodium phosphate monobasic monohydrate (0.45 mg), and sucrose (69.8 mg). After reconstitution with 5 mL of Sterile Water for Injection USP, the concentration is 1 mg/mL of gemtuzumab ozogamicin with a deliverable volume of 4.5 mL (4.5 mg).

12 CLINICAL PHARMACOLOGY

12.1 Mechanism of Action

Gemtuzumab ozogamicin is a CD33-directed antibody-drug conjugate (ADC). The antibody portion (hP67.6) recognizes human CD33 antigen. The small molecule, N-acetyl gamma calicheamicin, is a cytotoxic agent that is covalently attached to the antibody via a linker. Nonclinical data suggest that the anticancer activity of gemtuzumab ozogamicin is due to the binding of the ADC to CD33-expressing tumor cells, followed by internalization of the ADC-CD33 complex, and the intracellular release of N-acetyl gamma calicheamicin dimethyl hydrazide via hydrolytic cleavage of the linker. Activation of N-acetyl gamma calicheamicin dimethyl hydrazide induces double-strand DNA breaks, subsequently inducing cell cycle arrest and apoptotic cell death.

12.2 Pharmacodynamics

Saturation of a high percentage of CD33 antigenic sites is presumed to be required for maximum delivery of calicheamicin to leukemic blast cells. Near maximal peripheral CD33 saturation was observed across studies after gemtuzumab ozogamicin dosing at dose levels of 2 mg/m^2 and above.

At 9 mg/m^2 gemtuzumab ozogamicin (2 doses, 14 days apart), the risk for VOD increases as the Cmax of the first dose of gemtuzumab ozogamicin increases. The increase in VOD is more prominent in patients with prior stem cell transplantation.

12.3 Pharmacokinetics

There are no clinical PK data for the fractionated regimen. When gemtuzumab ozogamicin is administered at 9 mg/m^2 (2 doses, 14 days apart), the Cmax following the first dose for patients who received 9 mg/m^2 gemtuzumab ozogamicin was 3.0 mg/L and increased to 3.6 mg/L after the second dose.

Distribution

N-acetyl gamma calicheamicin dimethyl hydrazide is approximately 97% bound to human plasma proteins in vitro. Population PK analyses found the total volume of distribution of hP67.6 antibody (sum of V1 [6.31 L] and V2 [15.1 L]) to be approximately 21.4 L in patients.

Elimination

The clearance (CL) value of hP67.6 from plasma was 0.35 L/h after the first dose and 0.15 L/h after the second dose, a decrease of roughly 60%. The terminal plasma half-life (t½) for hP67.6 was 62 hours after the first dose and 90 hours after the second dose.

Metabolism

In vitro studies demonstrated that N-acetyl gamma calicheamicin dimethyl hydrazide is extensively metabolized, primarily via nonenzymatic reduction of the disulfide moiety.

Specific Populations

Age, race, sex, mild or moderate renal impairment (creatinine clearance [CLcr] 30–89 mL/min calculated by the Cockcroft-Gault equation) or mild hepatic impairment had no clinically significant effect on the pharmacokinetics of gemtuzumab ozogamicin. The pharmacokinetics of gemtuzumab ozogamicin in patients with severe renal impairment (CLcr 15–29 mL/min) or moderate (total bilirubin greater than 1.5× to 3.0× ULN) and severe hepatic impairment (total bilirubin greater than 3× ULN) is unknown.

Drug Interaction Studies

No clinical drug interaction studies have been performed.

In Vitro Studies

At clinically relevant concentrations, gemtuzumab ozogamicin had a low potential to:

- Inhibit CYP450 Enzymes: CYP1A2, CYP2A6, CYP2C8, CYP2C9, CYP2C19, CYP2D6, and CYP3A4/5.

At clinically relevant concentrations, N-acetyl gamma calicheamicin dimethyl hydrazide had a low potential to:

- Inhibit CYP450 Enzymes: CYP1A2, CYP2B6 , CYP2C8, CYP2C9, CYP2C19, CYP2D6, and CYP3A4/5.
- Induce CYP450 Enzymes: CYP1A2, CYP2B6, and CYP3A4.
- Inhibit UGT Enzymes: UGT1A1, UGT1A4, UGT1A6, UGT1A9, and UGT2B7.
- Inhibit Drug Transporters: P-gp (P-glycoprotein), breast cancer resistance protein (BCRP), organic anion transporter (OAT)1 and OAT3, organic cation transporter (OCT)2, and organic anion transporting polypeptide (OATP)1B1 and OATP1B3.

13 NONCLINICAL TOXICOLOGY

13.1 Carcinogenesis, Mutagenesis, Impairment of Fertility

Formal carcinogenicity studies have not been conducted with gemtuzumab ozogamicin. In toxicity studies, rats were dosed weekly for 6 weeks with gemtuzumab ozogamicin at doses up to 7.2 mg/m^2/week. After 6 weeks of dosing, rats developed oval cell hyperplasia in the liver, which is considered a potentially preneoplastic finding, at 7.2 mg/m^2/week (approximately 16 times the exposure in patients at the maximum recommended dose, based on AUC). Other preneoplastic or neoplastic changes observed with other antibody-calicheamicin conjugates in rats included basophilic and/or eosinophilic altered cell foci and hepatocellular adenomas. The relevance of these animal findings to humans is uncertain.

Gemtuzumab ozogamicin was clastogenic in vivo in the bone marrow of mice that received single doses greater than or equal to 22.1 mg/m^2. This is consistent with the known induction of DNA breaks by calicheamicin. N-acetyl gamma calicheamicin dimethyl hydrazide (the released cytotoxic agent) was mutagenic in the bacterial reverse mutation assay and clastogenic in the in vitro micronucleus assay in human TK6 cells.

In a female fertility study, female rats were administered daily intravenous doses of gemtuzumab ozogamicin up to 1.08 mg/m^2 for 14 days before mating with untreated male rats. Significant decreases in the numbers of corpora lutea and implants were observed at 1.08 mg/m^2, and dose-related decreases and increases in the number of live and dead embryos were observed at doses tested (approximately 0.4 times the exposure in patients at the maximum recommended dose, based on AUC). Increased embryofetal lethality at ≥0.36 mg/m^2 was observed in the presence of maternal toxicity that included decreases in gestational body weight and food consumption. Additional findings in female reproductive organs (ovarian atrophy and decreased numbers of follicles associated with atrophy of the uterus, vagina and mammary glands) occurred in rats and monkeys after dosing with other antibody-calicheamicin conjugates.

Fertility was assessed in male rats administered daily intravenous doses of gemtuzumab ozogamicin from 0.12 to 1.08 mg/m^2 for 28 days, followed by mating with untreated females, either at the end of the dosing period or after a 9-week drug-free period. Male fertility index was decreased at doses ≥0.12 mg/m^2 (approximately 1.2 times the exposure in patients at the maximum recommended dose, based on AUC). Effects on testes and epididymides occurred at ≥0.12 mg/m^2, including smaller size and lower weights in addition to adverse effects on sperm. Partial recovery was noted for some effects. Additional effects in male reproductive organs occurred in repeat-dose toxicology studies and included effects on mammary gland, testes, and epididymides in rats at ≥2.4 mg/m^2/week and effects on testes and epididymides in monkeys at 21.6 mg/m^2/week. Testicular effects in male monkeys with other antibody-calicheamicin conjugates included degeneration of seminiferous tubules and decreased epididymidal sperm, which did not reverse following a 6-week drug-free period.

14 CLINICAL STUDIES

14.1 Newly-Diagnosed CD33-positive AML

Study ALFA-0701

MYLOTARG in combination with chemotherapy was evaluated in ALFA-0701 (NCT00927498), a multicenter, randomized, open-label Phase 3 study of 271 patients with newly-diagnosed de novo AML ages 50 to 70 years. Patients were randomized (1:1) to receive induction therapy consisting of daunorubicin (60 mg/m^2 on Days 1 to 3) and cytarabine (200 mg/m^2 on Days 1 to 7) (DA) with (n=135) or without (n=136) MYLOTARG 3 mg/m^2 (up to maximum of one vial) on Days 1, 4, and 7. Patients who did not achieve a response after first induction could receive a second induction with daunorubicin and cytarabine alone (daunorubicin 35 mg/m^2/day on Days 1 and 2, and cytarabine 1 g/m^2 every 12 hours, on Day 1 to Day 3 without MYLOTARG). Patients with response received consolidation therapy with 2 courses of treatment including daunorubicin (60 mg/m^2 on Day 1 of consolidation course 1; 60 mg/m^2 on Days 1 and 2 of consolidation course 2) and cytarabine (1 g/m^2 every 12 hours on Days 1 to 4) with or without MYLOTARG 3 mg/m^2 (up to a maximum of one vial) on Day 1 according to their initial randomization. Patients who experienced remission were also eligible for allogeneic transplantation. An interval of at least 2 months between the last dose of MYLOTARG and transplantation was recommended.

The median age of the patients was 62 years (range, 50–70), 137 female and 134 male, and 88% had an Eastern Cooperative Oncology Group performance status (ECOG PS) of 0 to 1 at baseline. Baseline characteristics were balanced between treatment arms with the exception of gender as a higher percentage of males were enrolled in the MYLOTARG arm (55%) than in the DA alone arm (44%). Overall, 59%, 65%, and 70% of patients had documented favorable/intermediate risk and 33%, 27%, and 21% had poor/adverse disease by the National Comprehensive Cancer Network (NCCN), European LeukemiaNet (ELN), and cytogenetic risk classifications, respectively. CD33 expression on AML blasts by flow cytometry harmonized from local laboratory results was determined in 194/271 (72%) patients overall. Few patients (14%) had low CD33 expression (less than 30% of blasts), and none had no expression of CD33.

Efficacy was established on the basis of event-free survival (EFS), measured from the date of randomization until induction failure, relapse, or death by any cause. Per protocol, induction failure was defined as failure to achieve CR or CRp in induction, and date of induction failure was defined as date of marrow evaluation after the last course of induction. Median EFS was 17.3 months in the MYLOTARG arm versus 9.5 months in the control arm; hazard ratio (HR) 0.56 (95% CI: 0.42–0.76); 2-sided p less than 0.001 by log-rank test.

In an exploratory analysis of EFS defined as failure to achieve CR in induction, relapse, or death from any cause and using the date of randomization as the date of induction failure, median EFS was 13.6 months for MYLOTARG + DA and 8.8 months for DA with HR 0.68 (95% CI: 0.51–0.91).

The Kaplan-Meier plot for per-protocol EFS is shown in Figure 1. There was no statistically significant difference between treatment arms in overall survival.

Figure 1. Kaplan-Meier Plot of Event-Free Survival (mITT Population) ALFA-0701 Trial

Abbreviations: C=cytarabine; D=daunorubicin; GO=gemtuzumab ozogamicin; mITT=modified intent-to-treat.

Study AAML0531

MYLOTARG in combination with chemotherapy was evaluated in AAML0531 (NCT00372593), a multicenter, randomized study of 1,063 patients with newly-diagnosed AML ages 0 to 29 years. Patients were randomized to 5-cycle chemotherapy alone or with a single dose of MYLOTARG (3 mg/m^2/dose) administered once on Day 6 in Induction 1 and once on Day 7 in Intensification 2. All patients proceeded to Induction 2 regardless of remission status after Induction 1. In the absence of active disease, a neutrophil count (ANC) >1 Gi/L and a platelet count >75 Gi/L was recommended before proceeding with subsequent cycles of therapy. Patients not in remission after Induction 2 discontinued protocol therapy permanently. All other patients proceeded to Intensification 1. Patients with high- and intermediate-risk disease with 5/6 or 6/6 matched family donors (MFD) proceeded to HSCT following Intensification 1. Patients with high-risk disease proceeded to HSCT with an alternative donor if no MFD was available. All patients with low-risk disease and any high- and intermediate-risk patients without appropriate donors proceeded with Intensification 2 with or without MYLOTARG according to their initial randomization, followed by Intensification 3. All patients in remission were to proceed on to Intensification 2 or allogeneic HSCT. In Intensification 2, patients received MYLOTARG according to the initial randomization. Patients in remission after Intensification 2 proceeded to Intensification 3.

There were 532 patients randomized to treatment with MYLOTARG + chemotherapy and 531 to chemotherapy alone. Overall, 94% of patients were <18 years of age, and 6% were adults; median age was 9.0 years (range: 0–29 years). The patients were 49% male, 51% female, 73% White, 11% Black, 5% Asian, 11% other or missing race, and 18% Hispanic. The proportion of patients in each disease risk group: low risk (23% vs 23%), intermediate risk (57% vs 57%), and high risk (15% vs 17%).

Supportive evidence of efficacy was provided by event-free survival (EFS), measured from the date of study entry until induction failure, relapse, or death by any cause. Induction failure was defined as failure to achieve CR by the end of Induction 2 period, and date of induction failure was defined as Day 1 on study. The EFS hazard ratio was 0.84 (95% CI: 0.71–0.99). The estimated percentage of patients free of induction failure, relapse, or death at five years was 48% (95% CI: 43%–52%) in the MYLOTARG + chemotherapy arm versus 40% (95% CI: 36%–45%) in the chemotherapy alone arm.

The Kaplan-Meier plot for EFS is shown in Figure 2. No difference between treatment arms in overall survival was demonstrated.

Figure 2. Kaplan-Meier Plot of Event-Free Survival (Full Analysis Set) Study AAML0531 Trial

Abbreviations: GO=gemtuzumab ozogamicin.

Study AML-19

MYLOTARG single-agent therapy was evaluated in Study AML-19 (NCT00091234), a multicenter, randomized, open-label Phase 3 study comparing MYLOTARG to best supportive care (BSC) for patients with newly-diagnosed AML who were a) greater than 75 years of age or b) 61 to 75 years of age with a World Health Organization performance status (WHO PS) greater than 2 or were unwilling to receive intensive chemotherapy. Patients were randomized 1:1 and stratified by age (61–75 vs 76–80 years vs ≥81 years), CD33 positivity of bone marrow blasts (less than 20 % vs 20–80% vs greater than 80% vs unknown), initial white blood cell count (less than 30 vs greater than or equal to 30 × 10^9/L), WHO PS (0–1 vs 2 vs 3–4), and institution.

During induction, MYLOTARG 6 mg/m^2 was given on Day 1 and MYLOTARG 3 mg/m^2 was given on Day 8. Patients with no evidence of disease progression or significant toxicities after MYLOTARG induction received continuation therapy as outpatients with up to 8 courses of treatment including MYLOTARG 2 mg/m^2 on Day 1 every 4 weeks. Patients continued therapy if they did not experience significant toxicities, relapse, or disease progression. BSC included standard supportive care measures and hydroxyurea or other anti-metabolites for palliative purposes.

In total, 118 patients were randomized to treatment with MYLOTARG and 119 patients to BSC. Overall, the median age of patients was 77 years (range, 62–88 years), and most patients (65%) had a WHO PS of 0 to 1 at baseline. Baseline characteristics were balanced between treatment arms with the exception of gender and cytogenetics. Compared to the BSC arm, the MYLOTARG arm had a higher percentage of females (52% vs 39%) and patients with favorable/intermediate risk cytogenetics (50% vs 38%). The proportion with adverse cytogenetics was similar between arms (28% vs 27%). Fewer patients on the MYLOTARG arm had missing cytogenetics data (22% vs 35%). CD33 expression on AML blasts by flow cytometry at a centralized location was determined in 235/237 (99%) patients; 10% had CD33 expression less than 20%.

The efficacy of MYLOTARG was established on the basis of improvement in overall survival (OS). The hazard ratio (HR) for OS was 0.69 (95% CI: 0.53–0.90) (2-sided p=0.005 by log-rank test). Median OS was 4.9 months in the MYLOTARG arm versus 3.6 months in the control arm.

14.2 Relapsed or refractory CD33-positive AML

Study MyloFrance-1

The efficacy of MYLOTARG as a single agent was evaluated in MyloFrance-1 a phase 2, single-arm, open-label study in adults with CD33-positive AML in first relapse. Patients with secondary leukemia or a prior autologous or allogeneic stem cell transplantation were excluded. Study treatment included a single course of MYLOTARG 3 mg/m^2 on Days 1, 4, and 7. Consolidation therapy consisted of cytarabine intravenously every 12 hours for 3 days. The cytarabine dose was 3 g/m^2 for patients less than 55 years old and 1 g/m^2 for patients 55 years or older and/or patients with a creatinine clearance below 50 mL/minute. Hematopoietic stem cell transplantation (HSCT) was allowed after treatment with MYLOTARG, but it was recommended to delay HSCT by at least 90 days following MYLOTARG.

There were 57 patients treated with MYLOTARG. Overall, the median age of patients was 64 years (range 22–80 years). The median duration of first remission was 10 months. Forty-four (78%) patients had intermediate-risk and 12 (22%) poor-risk cytogenetics.

The efficacy of MYLOTARG was established on the basis of complete remission (CR) rate and duration of remission. Fifteen (26%; 95% CI 16% – 40%) patients achieved CR following a single course of MYLOTARG. Median relapse-free survival, measured from the first documentation of CR to the date of relapse or death, was 11.6 months.

15 REFERENCES

1. OSHA Hazardous Drugs. OSHA. http://www.osha.gov/SLTC/hazardousdrugs/index.html

16 HOW SUPPLIED/STORAGE AND HANDLING

MYLOTARG (gemtuzumab ozogamicin) for injection is a white to off-white lyophilized cake or powder supplied in a carton (NDC 0008-4510-01) containing one 4.5 mg single-dose vial [see Dosage and Administration (2)].

STORAGE AND HANDLING

Refrigerate (2°C to 8°C; 36°F to 46°F) MYLOTARG vials and store in the original carton to protect from light. DO NOT FREEZE.

MYLOTARG is a cytotoxic drug. Follow applicable special handling and disposal procedures.^1

17 PATIENT COUNSELING INFORMATION

Hepatotoxicity, Including Veno-occlusive Liver Disease (VOD)

Inform patients that liver problems, including severe, life-threatening, or fatal VOD may develop during MYLOTARG treatment. Prior to receiving MYLOTARG, inform patients who previously received, or will receive an HSCT that they may be at increased risk for developing VOD. Inform patients that the risk of developing VOD after an allogeneic HSCT is increased after receiving treatment with MYLOTARG. Inform patients that signs or symptoms of liver toxicity, including rapid weight gain, right upper quadrant pain and tenderness, hepatomegaly, and ascites should be monitored regularly during treatment, but these symptoms may not identify all patients at risk or prevent the complications of liver toxicity. Inform patients that liver problems may require dosing interruption or permanent discontinuation of MYLOTARG [see Warnings and Precautions (5.1)].

Hemorrhage

Inform patients that decreased platelet counts, which may be life-threatening, may develop during MYLOTARG treatment and that complications associated with decreased platelet counts may include bleeding/hemorrhage events, which may be life-threatening or fatal. Inform patients to report signs and symptoms of bleeding/hemorrhage during treatment with MYLOTARG. Inform patients that severe bleeding/hemorrhage may require dosing interruption or permanent discontinuation of MYLOTARG [see Warnings and Precautions (5.3)].

Infusion-Related Reactions

Advise patients to contact their health care provider if they experience signs and symptoms of infusion-related reactions, including symptoms such as fever, chills, rash, or breathing problems [see Warnings and Precautions (5.2)].

Embryo-Fetal Toxicity

Advise pregnant women of the potential risk to the fetus. Advise females of reproductive potential to inform their healthcare provider of a known or suspected pregnancy [see Warnings and Precautions (5.6), Use in Specific Populations (8.1)].

Advise females of reproductive potential to use effective contraception during treatment with MYLOTARG and for at least 6 months after the last dose [see Use in Specific Populations (8.3)].

Advise males with female partners of reproductive potential to use effective contraception during treatment with MYLOTARG and for at least 3 months after the last dose [see Use in Specific Populations (8.3)].

Lactation

Advise women not to breastfeed during treatment with MYLOTARG and for at least 1 month after the final dose [see Use in Specific Populations (8.2)].

Infertility

Advise males and females of reproductive potential that MYLOTARG may impair fertility [see Use in Specific Populations (8.3)].

This product's labeling may have been updated. For the most recent prescribing information, please visit www.pfizer.com.

US License No. 003

LAB-0868-8.0

PRINCIPAL DISPLAY PANEL - 4.5 mg Vial Label

Pfizer

NDC 0008-4510-01
Rx only

MYLOTARG™
(gemtuzumab ozogamicin)
for Injection

4.5 mg/vial

For Intravenous Infusion Only

Single-dose vial.

No Preservatives
Discard unused portion.

PRINCIPAL DISPLAY PANEL - 4.5 mg Vial Carton

Pfizer

NDC 0008-4510-01

MYLOTARG™
(gemtuzumab ozogamicin)
for Injection

4.5 mg/vial

For Intravenous Infusion Only

Reconstitution and dilution
required

No Preservatives

One Single-Dose Vial.
Discard unused portion.

Rx only